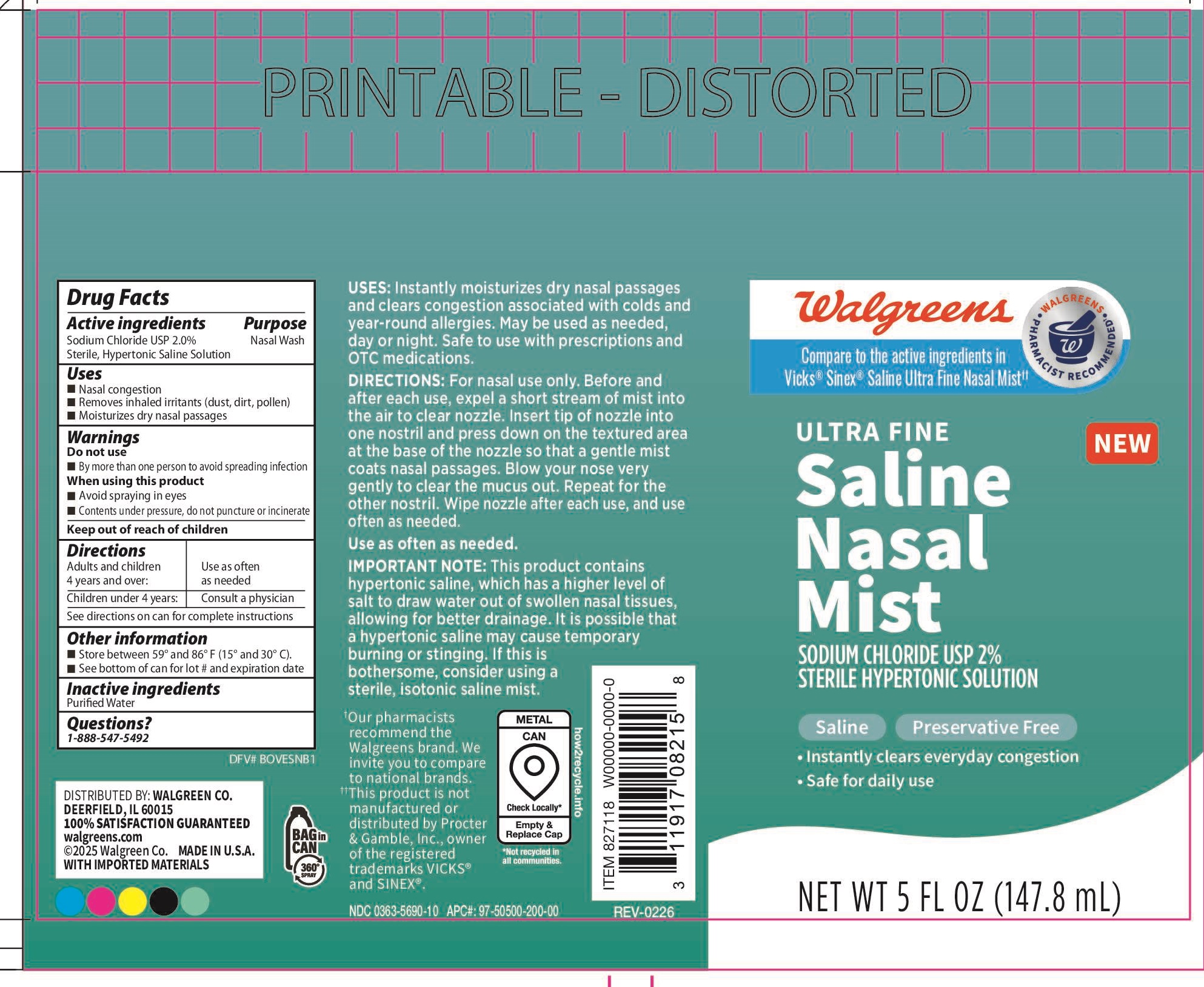 DRUG LABEL: Walgreens ULTRA FINE MOISTURIZING SALINE MIST
NDC: 0363-5690 | Form: AEROSOL, SPRAY
Manufacturer: WALGREEN COMPANY
Category: otc | Type: HUMAN OTC DRUG LABEL
Date: 20260210

ACTIVE INGREDIENTS: SODIUM CHLORIDE 2 g/100 mL
INACTIVE INGREDIENTS: WATER

Active ingredient

Sodium Chloride 2.0%

Purpose

Nasal Wash

Uses

- Nasal congestion
- removes inhaled irritants- dust, dirt, pollen
- moisturizes dry nasal passages

Warnings

Do not use

- By more than one person to avoid spreading infection

When Using this product.

- Avoid spraying in eyes.
- Content under pressure.
- Do not puncture or incinerate.

Directions

Read HOW TO USE instructions before use

- Adults and children 4 years of age an older:Use as often as needed or as directed by a physician
- Children under 4 years: Consult a physician.

Other information

- Do not use if the printed safety seal on the bottle is broken or missing.
- Store between 59º and 86º F (15º and 30º C)
- See bottom of can for lot number and expiration date

Inactive ingredients

Purified Water